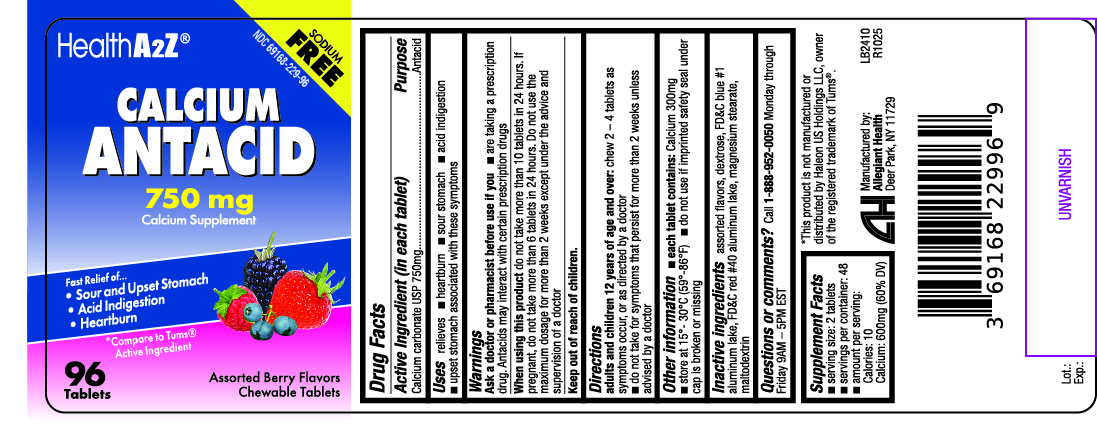 DRUG LABEL: Calcium Antacid
NDC: 69168-229 | Form: TABLET, CHEWABLE
Manufacturer: Allegiant Health
Category: otc | Type: HUMAN OTC DRUG LABEL
Date: 20171117

ACTIVE INGREDIENTS: CALCIUM CARBONATE 750 mg/1 1
INACTIVE INGREDIENTS: DEXTROSE; FD&C BLUE NO. 1; FD&C RED NO. 40; MAGNESIUM STEARATE; MALTODEXTRIN

Drug Facts

Active ingredient (in each tablet)

Calcium Carbonate USP 750mg

Purpose

Antacid

Uses

relieves

- heartburn
- sour stomach
- acid indigestion
- upset stomach associated with these symptoms

Ask a doctor or pharmacist before use if you

- have kidney disease
- are taking a prescription drug. Antacids may interact with certain prescription drugs

When using this product

- do not take more than 10 tablets in 24 hours
- If pregnant, do not take more than 6 tablets in 24 hours
- do not use the maximum dosage for more than 2 weeks except under the advice and supervision of a doctor

Directions

- adults and children 12 years of age and over: chew 2 – 4 tablets as symptoms occur, or as directed by a doctor
- do not take for symptoms that persist for more than 2 weeks unless advised by a doctor

Other Information

- each tablet contains: calcium 300mg
- store at 15º-30ºC (59º-86ºF)
- do not use if imprinted safety seal under cap is broken or missing

Supplement Facts

- Serving size 2 tablets
- Servings per Container: 48
- Amount Per Serving
  Calories: 10
  Calcium: 600 mg (60%DV)

Inactive Ingredients

assorted flavors, dextrose, FD&C blue #1 aluminum lake, FD&C red #40 aluminum lake, magnesium stearate, maltodextrin

Package/Label Principal Display Panel

SODIUM FREE

HealthA2Z®

CALCIUM ANTACID

750 mg
Calcium Carbonate 750mg

Calcium Supplement

Fast Relief of...

- Sour and Upset Stomach
- Acid Indigestion
- Heartburn

*Compare to Tums Active Ingredient

Tablets

Assorted Berry Flavors

Chewable Tablets